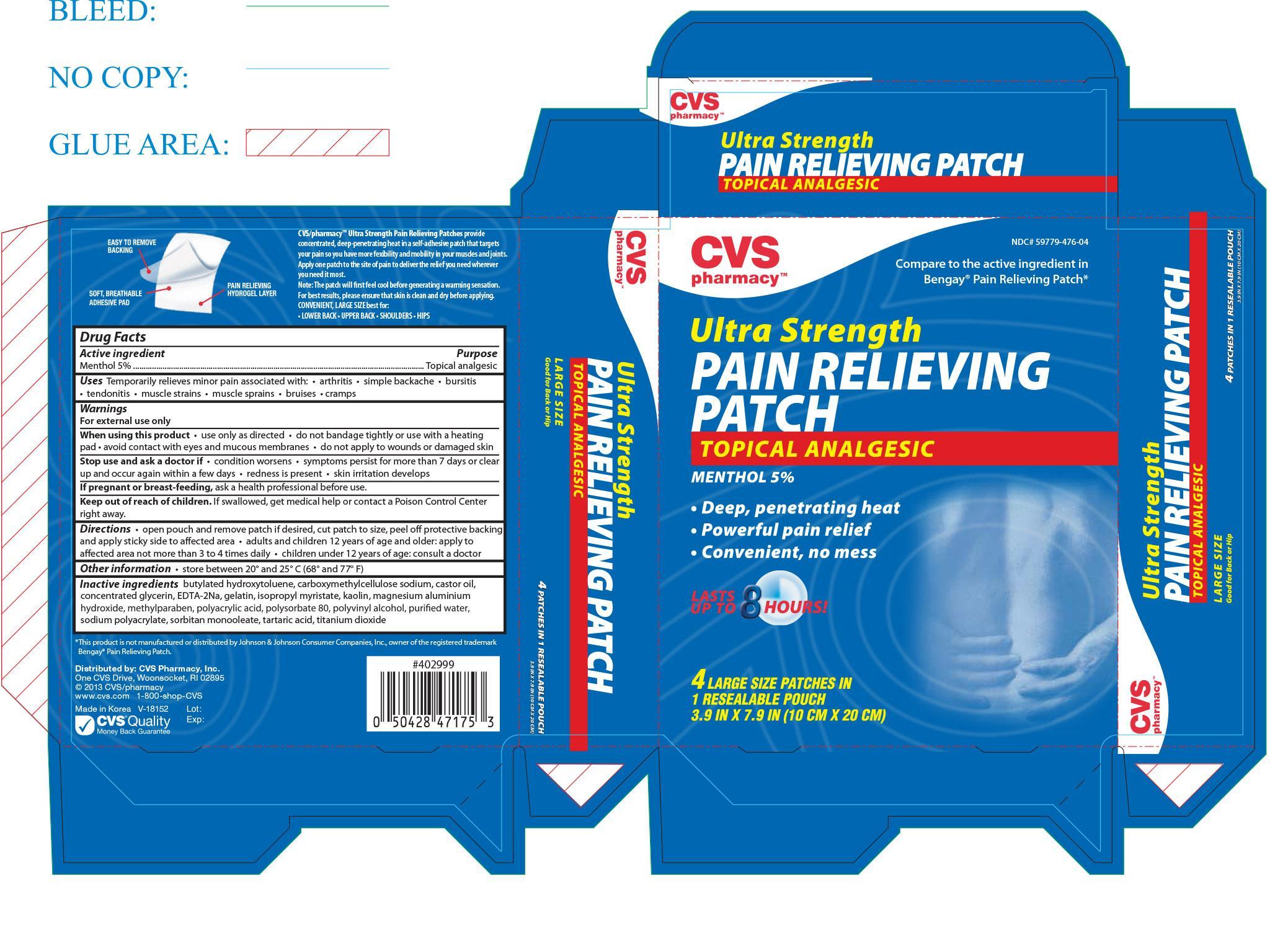 DRUG LABEL: CVS Ultra Strength Pain Relieving
NDC: 59779-476 | Form: PATCH
Manufacturer: CVS Pharmacy, Inc.
Category: otc | Type: HUMAN OTC DRUG LABEL
Date: 20151203

ACTIVE INGREDIENTS: MENTHOL 750 mg/1 1
INACTIVE INGREDIENTS: BUTYLATED HYDROXYTOLUENE; CARBOXYMETHYLCELLULOSE SODIUM; CASTOR OIL; GELATIN; ISOPROPYL MYRISTATE; KAOLIN; METHYLPARABEN; POLYSORBATE 80; POLYVINYL ALCOHOL; WATER; SORBITAN MONOOLEATE; TARTARIC ACID; TITANIUM DIOXIDE

Drug Facts

Active ingredient Purpose

Menthol 5% Topical Analgesic

PURPOSE

Uses Temporarily relieves minor pain associated with:

- arthritis
- simple backache
- bursitis
- tendonitis
- muscle strains
- muscle sprains
- bruises cramps

Warnings

For external use only

When using this product

- use only as directed
- do not bandage tightly or use with a heating pad
- avoid contact with eyes and mucous membranes
- do not apply to wounds or damaged skin

Stop use and ask a doctor if

- condition worsens
- symptoms persist for more than 7 days or clear up and occur again within a few days
- redness is present
- skin irritation develops

PREGNANCY OR BREAST FEEDING

If pregnant or breast-feeding, ask a health professional before use.

Keep out of reach of children. If swallowed, get medical help or contact a Poison Control Center right away.

Directions

- open pouch and remove patch if desired, cut patch to size, peel off protective backing and apply sticky side to affected area
- adults and children 12 years of age and older: apply to affected area not more than 3 to 4 times daily
- children under 12 years of age: consult a doctor

Other information

- store between 20° and 25° C (68° and 77°F)

INACTIVE INGREDIENT

Inactive ingredients butylated hydroxytoluene, carboxymethylcellulose sodium, caster oil, concentrated glycerin, EDTA-2Na, gelatin, isopropyl myristate, kaolin, magnesium aluminium hydroxide, methylparaben, polyacrylic acid, polysorbate 80, polyvinyl alcohol, purified water, sodium polyacrylate, sorbitan monooleate, tartaric acid, titanium dioxide

DOSAGE AND ADMINISTRATION

Distributed By:

CVS Pharmacy, Inc.

One CVS Drive.

Woonsocket, RI 02895

Made in Korea